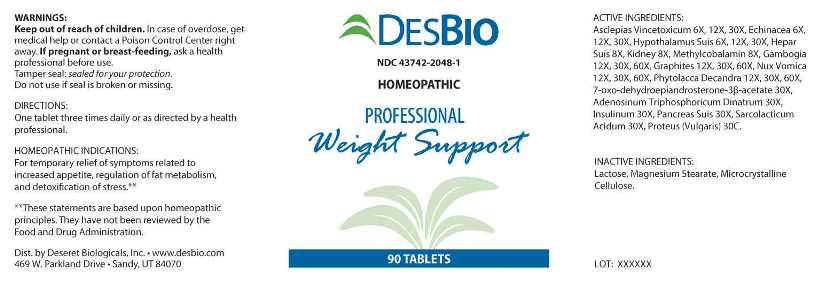 DRUG LABEL: Professional Weight Support
NDC: 43742-2048 | Form: TABLET
Manufacturer: Deseret Biologicals
Category: homeopathic | Type: HUMAN OTC DRUG LABEL
Date: 20240117

ACTIVE INGREDIENTS: VINCETOXICUM HIRUNDINARIA ROOT 6 [hp_X]/1 1; ECHINACEA, UNSPECIFIED 6 [hp_X]/1 1; SUS SCROFA HYPOTHALAMUS 6 [hp_X]/1 1; PORK LIVER 8 [hp_X]/1 1; PORK KIDNEY 8 [hp_X]/1 1; METHYLCOBALAMIN 8 [hp_X]/1 1; GAMBOGE 12 [hp_X]/1 1; GRAPHITE 12 [hp_X]/1 1; STRYCHNOS NUX-VOMICA SEED 12 [hp_X]/1 1; PHYTOLACCA AMERICANA ROOT 12 [hp_X]/1 1; 7-KETO-DEHYDROEPIANDROSTERONE 30 [hp_X]/1 1; ADENOSINE TRIPHOSPHATE DISODIUM 30 [hp_X]/1 1; INSULIN HUMAN 30 [hp_X]/1 1; SUS SCROFA PANCREAS 30 [hp_X]/1 1; LACTIC ACID, L- 30 [hp_X]/1 1; PROTEUS VULGARIS 30 [hp_C]/1 1
INACTIVE INGREDIENTS: LACTOSE MONOHYDRATE; MAGNESIUM STEARATE; CELLULOSE, MICROCRYSTALLINE

DRUG FACTS:

ACTIVE INGREDIENTS:

Asclepias Vincetoxicum 6X, 12X, 30X, Echinacea (Angustifolia) 6X, 12X, 30X, Hypothalamus (Suis) 6X, 12X, 30X, Hepar Suis 8X, Kidney (Suis) 8X, Methylcobalamin 8X, Gambogia 12X, 30X, 60X, Graphites 12X, 30X, 60X, Nux Vomica 12X, 30X, 60X, Phytolacca Decandra 12X, 30X, 60X, 7-Oxo-Dehydroepiandrosterone 3β-Acetate 30X, Adenosinum Triphosphoricum Dinatrum 30X, Insulinum (Human) 30X, Pancreas Suis 30X, Sarcolacticum Acidum 30X, Proteus (Vulgaris) 30C.

INDICATIONS:

For temporary relief of symptoms related to increased appetite, regulation of fat metabolism, and detoxification of stress.**

**These statements are based upon homeopathic principles. They have not been reviewed by the Food and Drug Administration.

WARNINGS:

Keep out of reach of children. In case of overdose, get medical help or contact a Poison Control Center right away.

If pregnant or breast-feeding, ask a health professional before use.

Tamper seal: Sealed for your protection.

Do not use if seal is broken or missing.

Keep out of reach of children. In case of overdose, get medical help or contact a Poison Control Center right away.

DIRECTIONS:

One tablet three times daily or as directed by a health professional.

INDICATIONS:

For temporary relief of symptoms related to increased appetite, regulation of fat metabolism, and detoxification of stress.**

**These statements are based upon homeopathic principles. They have not been reviewed by the Food and Drug Administration.

INACTIVE INGREDIENTS:

Lactose, Magnesium Stearate, Microcrystalline Cellulose.

QUESTIONS:

Dist. by Deseret Biologicals Inc. • www.desbio.com

469 W. Parkland Drive • Sandy, UT 84070

PACKAGE LABEL DISPLAY:

DESBIO

NDC 43742-2048-1

HOMEOPATHIC

PROFESSIONAL

Weight Support

90 TABLETS